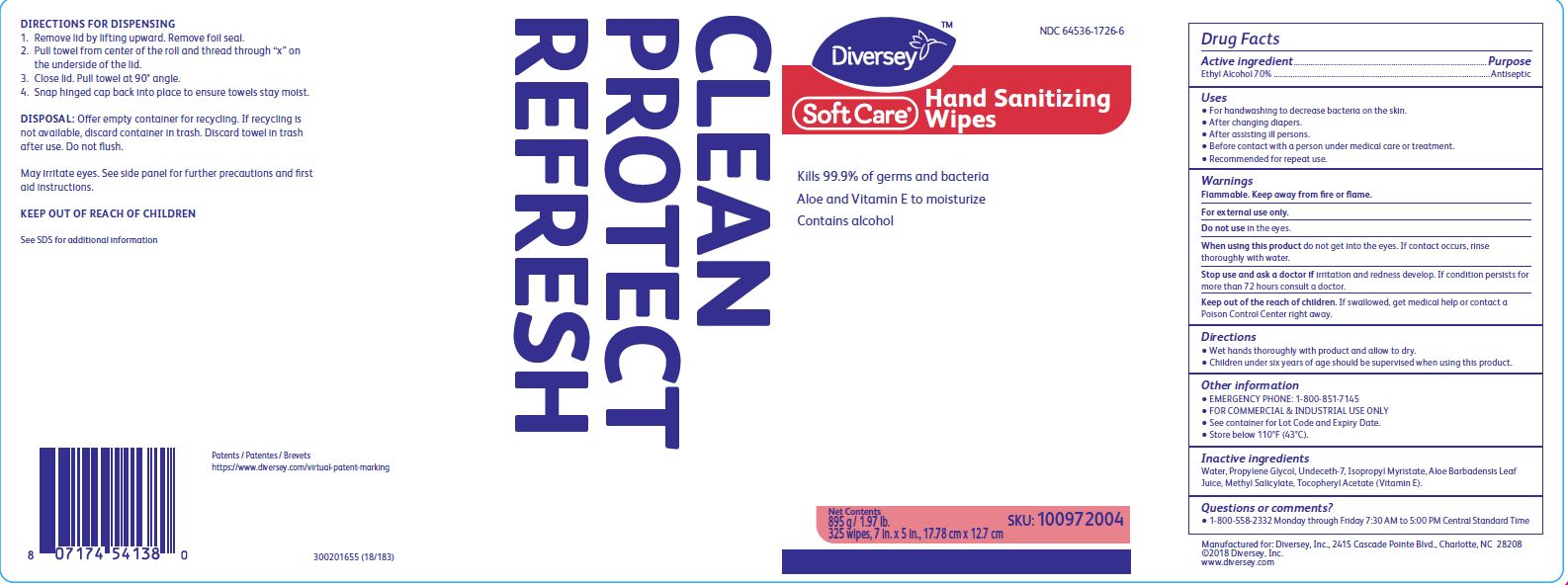 DRUG LABEL: Soft Care Hand Sanitizing Wipes
NDC: 64536-1726 | Form: CLOTH
Manufacturer: Diversey, Inc.
Category: otc | Type: HUMAN OTC DRUG LABEL
Date: 20241216

ACTIVE INGREDIENTS: ALCOHOL 70 g/100 g
INACTIVE INGREDIENTS: WATER; PROPYLENE GLYCOL; METHYL SALICYLATE; UNDECETH-7; .ALPHA.-TOCOPHEROL ACETATE; ISOPROPYL MYRISTATE; ALOE VERA LEAF

Soft Care Hand Sanitizing Wipes

Active ingredient

Ethyl Alcohol 70%

Purpose

Antiseptic

Uses

- For handwashing to decrease bacteria on the skin.
- After changing diapers.
- After assisting ill persons.
- Before contact with a person under medical care or treatment.
- Recommended for repeat use.

Warnings

Flammable. Keep away from fire or flame.

For external use only.

Do not usein the eyes.

WHEN USING

When using this productdo not get into the eyes. If contact occurs, rinse thoroughly with water.

Stop use and ask a doctor ifirritation and redness develop. If condition persists for more than 72 hours consult a doctor.

KEEP OUT OF REACH OF CHILDREN

Keep out of the reach of children.If swallowed, get medical help or contact a Poison Control Center right away.

KEEP OUT OF REACH OF CHILDREN

Keep out of the reach of children.If swallowed, get medical help or contact a Poison Control Center right away.

Directions

- Wet hands thoroughly with product and allow to dry.
- Children under six years of age should be supervised when using this product.

Other information

- EMERGENCY PHONE: 1-800-851-7145
- FOR COMMERCIAL and INDUSTRIAL USE ONLY
- See container for Lot Code and Expiry Date.
- Store below 110 F (43 C)

Inactive ingredients

Water, Propylene Glycol, Undeceth-7, Isopropyl Myristate, Aloe Barbadensis Leaf Juice, Methyl Salicylate, Tocopheryl Acetate (Vitamin E).

Questions or comments?

- 1-800-558-2332 Monday through Friday 7:30 AM to 5:00 PM Central Standard Time

PACKAGE LABEL

NDC 64536-1726-6

Diversey

SoftCare Hand Sanitizing Wipes

Kills 99.9% of germs and bacteria

Aloe and Vitamin E to moisturize

Contains alcohol

CLEAN

PROTECT

REFRESH

Net Contents

895g / 1.97 lb.

325 wipes, 7 in. x 5 in., 17.78 cm x 12.7 cm

SKU: 100972004